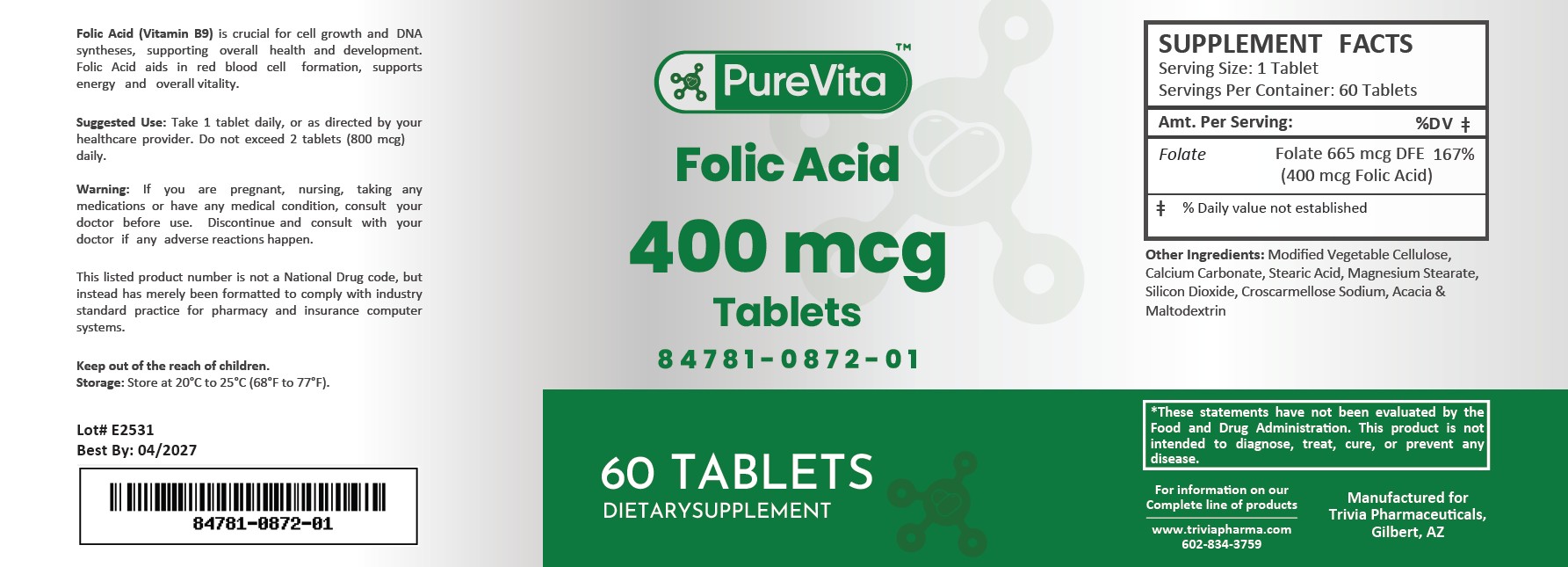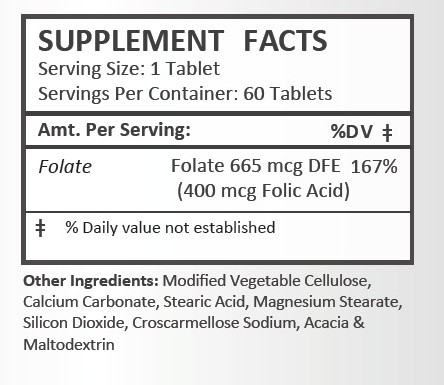 DRUG LABEL: Folic Acid
NDC: 84781-872 | Form: TABLET
Manufacturer: Trivia Pharmaceuticals, LLC
Category: other | Type: DIETARY SUPPLEMENT
Date: 20250703

ACTIVE INGREDIENTS: FOLIC ACID 400 ug/1 1

Folic Acid 400mcg

Health Claim Section:

Folic Acid 400 mcg Tablets

Description:

Folic Acid (Vitamin B9) is crucial for cell growth and DNA syntheses, supporting overall health and development. Folic Acid aids in red blood cell formation, supports energy and overall vitality.

This listed product is not a National Drug Code, but instead has merely been formatted to comply with standard industry practice for pharmacy and insurance computer systems.

Warnings and Precautions:

This product is contraindicated in patients with a known hypersensitivity to any of the ingredients.

Keep out of the reach of children.

If you are pregnant, nursing, taking any medications or have any medical condition, consult with your doctor before use. Discontinue and consult with your doctor if any adverse reactions happen.

Dosage and Administration:

Take 1 tablet daily, or as directed by your healthcare provider. Do not exceed 2 tablets (800 mcg) daily.

How Supplied:

Folic Acid 400 mcg tablets are supplied as yellow, round tablets in plastic bottles of 60 ct.

84781-872-01

These statements have not been evaluated by the Food and Drug Administration. This product is not intended to diagnose, treat, cure or prevent any disease.

All prescriptions using this product shall be pursuant to state statutes as applicable. This is not an Orange Book product. There are no implied or explicit claims on therapeutic equivalence.

Manufactured for:
Trivia Pharmaceuticals

Gilbert, AZ

Storage:

Store at room temperature 20° - 25°C (68° - 77°F)